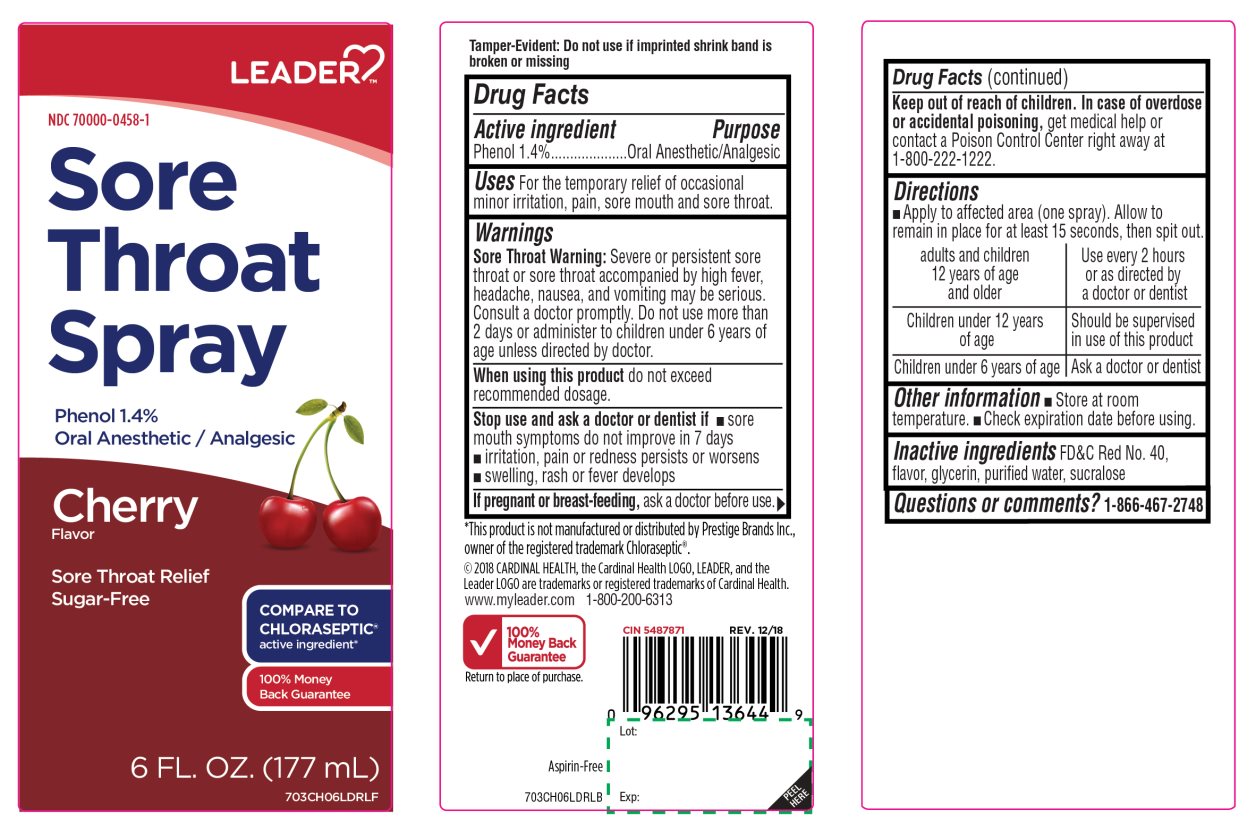 DRUG LABEL: Sore Throat Relief

NDC: 70000-0458 | Form: SPRAY
Manufacturer: Cardinal Health
Category: otc | Type: HUMAN OTC DRUG LABEL
Date: 20251014

ACTIVE INGREDIENTS: PHENOL 1.4 g/100 mL
INACTIVE INGREDIENTS: FD&C RED NO. 40; GLYCERIN; WATER; SUCRALOSE

Sore Throat Relief Cherry Flavor Drug Facts

Active ingredient

Phenol 1.4%

Purpose

Oral Anesthetic/Analgesic

Uses

For the temporary relief of occasional minor irritation, pain, sore mouth and sore throat.

Warnings

Sore throat warning:Severe or persistent sore throat or sore throat that accompanied by high fever, headache, nausea, and vomiting may be serious. Consult a doctor promptly. Do not use more than 2 days or administer to children under 6 years of age unless directed by a doctor.

When using this product,

do not exceed recommended dose.

Stop use and ask a doctor or dentist if

- sore mouth symptoms do not improve in 7 days
- irritation, pain or redness persists or worsens
- swelling, rash or fever develops

If pregnant or breast-feeding,

ask a doctor before use.

Keep out of reach of children.

In case of overdose or accidental poisoning, get medical help or contact a Poison Control Center right away (1-800-222-1222).

Directions

- Apply to affected area (one spray). Allow to remain in place for at least 15 seconds, then spit out.

Adults and children 12 year of age and older | Use every 2 hours or as directed by a doctor or dentist
Children under 12 years of age | Should be supervised in use of this product
Children under 6 years of age | Ask a doctor or dentist

Other information

- Store at room temperature
- Check expiration date before using.

Inactive ingredients

FD&C Red No. 40, flavor, glycerin, purified water, sucralose.

Questions or comments?

1-866-467-2748

Principal Display Panel

NDC# 70000-0458-1

Sore Throat Spray

Phenol 1.4%

Oral Anesthetic / Analgesic

Cherry Flavor

Sore Throat Relief

Sugar-Free

6 FL. OZ. (177 mL)

100% Money Back Guarantee

Return to place of purchase.

Aspirin-Free

COMPARE TO CHLORASEPTIC® active ingredient*

TAMPER EVIDENT: Do not use if imprinted shrink band is broken or missing.

*This product is not manufactured or distributed by Prestige Brands, Inc., owner of the registered trademark Chloraseptic®.

©2018 CARDINAL HEALTH, the Cardinal Health LOGO, LEADER and the Leader LOGO are trademark or registered trademarks of Cardinal Health.

www.myleader.com1-800-200-6313